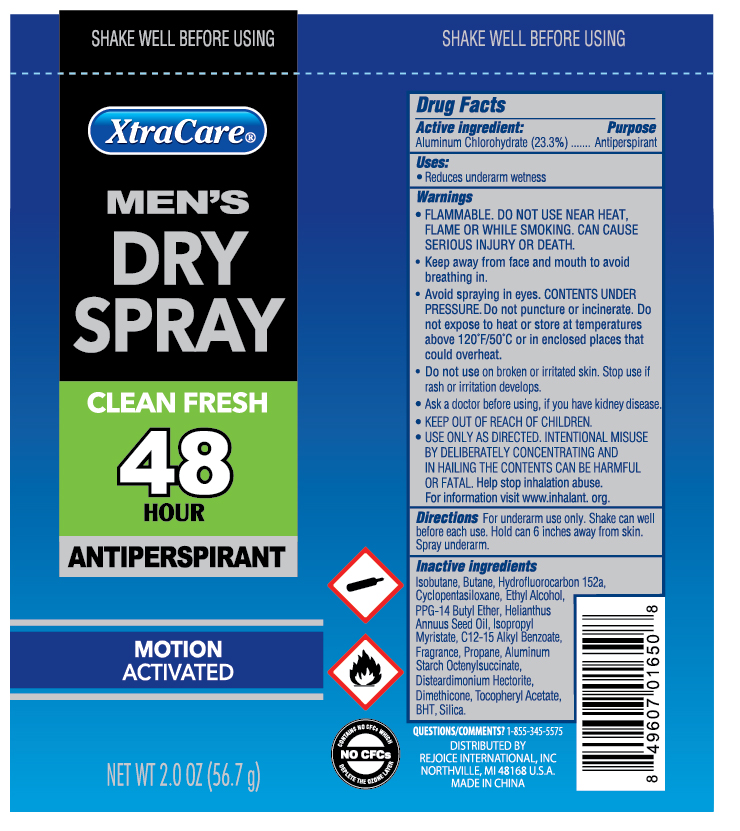 DRUG LABEL: Antiperspirant Dry 2 oz Men
NDC: 57337-091 | Form: AEROSOL, SPRAY
Manufacturer: Rejoice International Inc
Category: otc | Type: HUMAN OTC DRUG LABEL
Date: 20190913

ACTIVE INGREDIENTS: ALUMINUM CHLOROHYDRATE 23 g/100 g
INACTIVE INGREDIENTS: SILICON DIOXIDE; ISOPROPYL MYRISTATE; ALUMINUM STARCH OCTENYLSUCCINATE; DISTEARDIMONIUM HECTORITE; DIMETHICONE; CYCLOMETHICONE 5; PPG-14 BUTYL ETHER; ALKYL (C12-15) BENZOATE; ALCOHOL; BUTYLATED HYDROXYTOLUENE; ISOBUTANE; 1,1-DIFLUOROETHANE; SUNFLOWER OIL; PROPANE

Antiperspirant Dry 2 oz Men

Active Ingredient ........................................................................... Purpose

Aluminum Chlorohydrate 23.3% .................................................. Antiperspirant

PURPOSE

Antiperspirant

Keep out of reach of children. If swallowed, get medical help or contact a Poison Control Center immediately. Do not use on children under 2 years of age unless directed by a doctor.

INDICATIONS AND USAGE

Reduces underarm wetness

Warnings

For external use only.

Flammable. Do not use while smoking or near heat or flame or while smoking. Can cause serious injury or death.

- Keep away from face and mouth to avoid breathing in.
- Avoid spraying in eyes. CONTENTS UNDER PRESSURE. Do not puncture or incinerate. Do not expose to heat or store at temperatures above 120oF/50oC or in enclosed places that could overheat.
- Do not use on broken or irrated skin. Stop use if rash or irritation develops.
- Ask a doctor before using, if you have kidney disease.
- KEEP OUT OF REACH OF CHILDREN.
- USE ONLY AS DIRECTED. INTENTIONAL MISSUSE BY DELIBERATELY CONCENTRATING AND INHAILING THE CONTENTS CAN BE HARMFUL OR FATAL. Help stop inhalation abuse. For more information visit www.inhalant.org

Directions

- For underarm use only. Shake can well before each use. Hold can 6 inches away from skin. Spray underarm.

Inactive Ingredients

Isobutane, Butane, Hydrofluorocarbon 152a, Cyclopentasiloxane, Ethyl Alcohol, PPG-14 Butyl Ether, Helianthus Annuus Seed Oil, Isopropryl Myristate, C12-15 Alkyl Benzoate, Frangrance, Propane, Aluminum Starch Ocetenylsuccinate, Disteardimonium Hectorite, Dimethicone, Tocopheryl Acetate, BHT, Silica